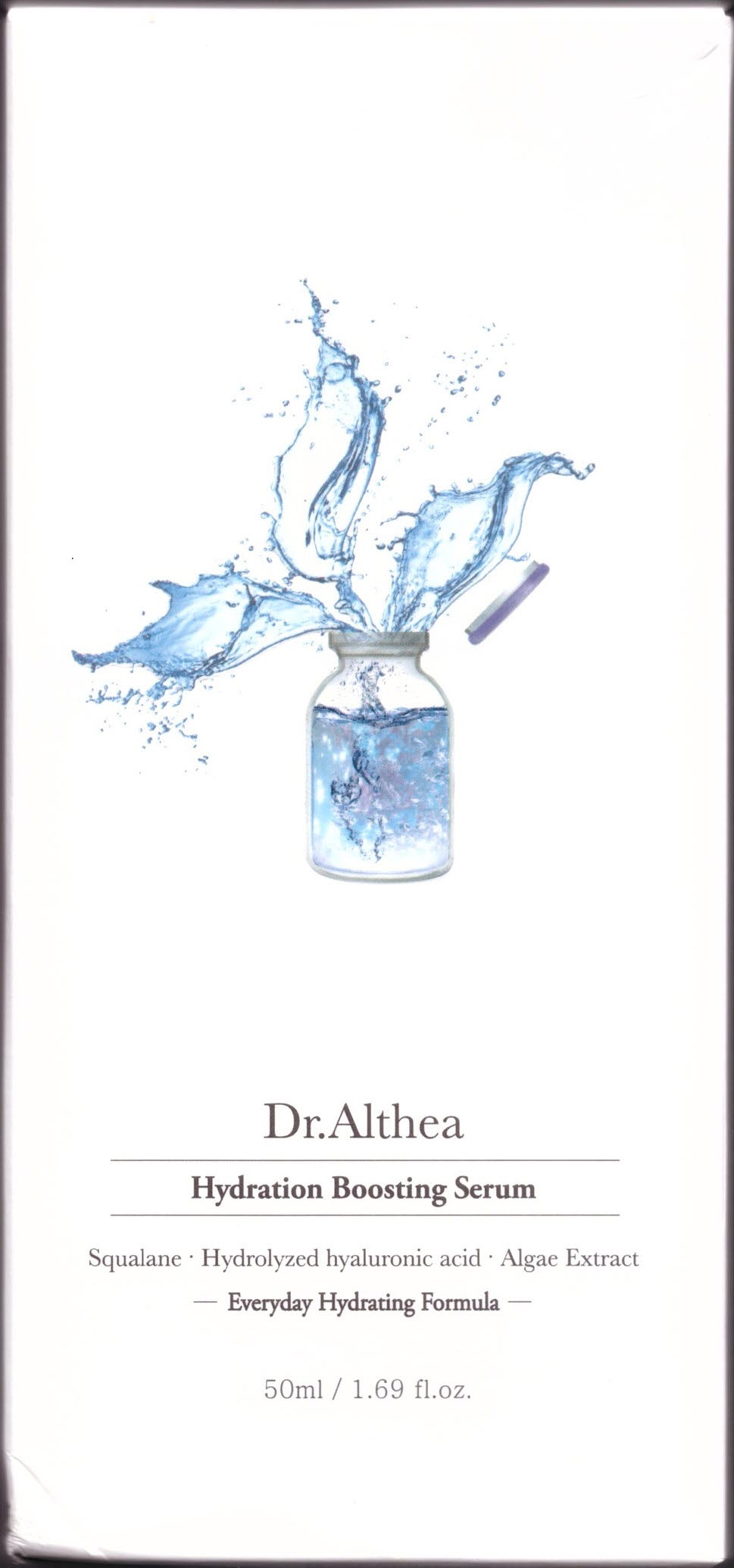 DRUG LABEL: DR.ALTHEA HYDRATION BOOSTING SERUM
NDC: 70905-0003 | Form: CREAM
Manufacturer: Dr. Althea
Category: otc | Type: HUMAN OTC DRUG LABEL
Date: 20160812

ACTIVE INGREDIENTS: DIMETHICONE 2 g/100 mL
INACTIVE INGREDIENTS: WATER; BUTYLENE GLYCOL

Drug Facts

ACTIVE INGREDIENT

DIMETHICONE

INACTIVE INGREDIENT

SQUALANE,HYDROLYZED HYALURONIC ACID,ALGAE EXTRACT,WATER,BUTYLENE GLYCOL,ETC

PURPOSE

Helps Hydrate skin

keep out of reach of the children

INDICATIONS AND USAGE

After using a skin toner, apply this product to skin and spread it over skin evenly once or twice every morning and night.

WARNINGS

1. If the following symptoms occur after product use, stop using the product immediately and consult a dermatologist (continuous use can exacerbate the symptoms).
1) Occurrence of red spots, swelling, itchiness, and other skin irritation
2) If the symptoms above occur after the application area is exposed to direct sunlight
2. Do not use on open wounds, eczema, and other skin irritations
3. Precaution for Storage and Handling
1) Close the lid after use
2) Keep out of reach of infants and children
3) Do not to store in a place with high/low temperature and exposed to direct sunlight

DOSAGE AND ADMINISTRATION

for external use only